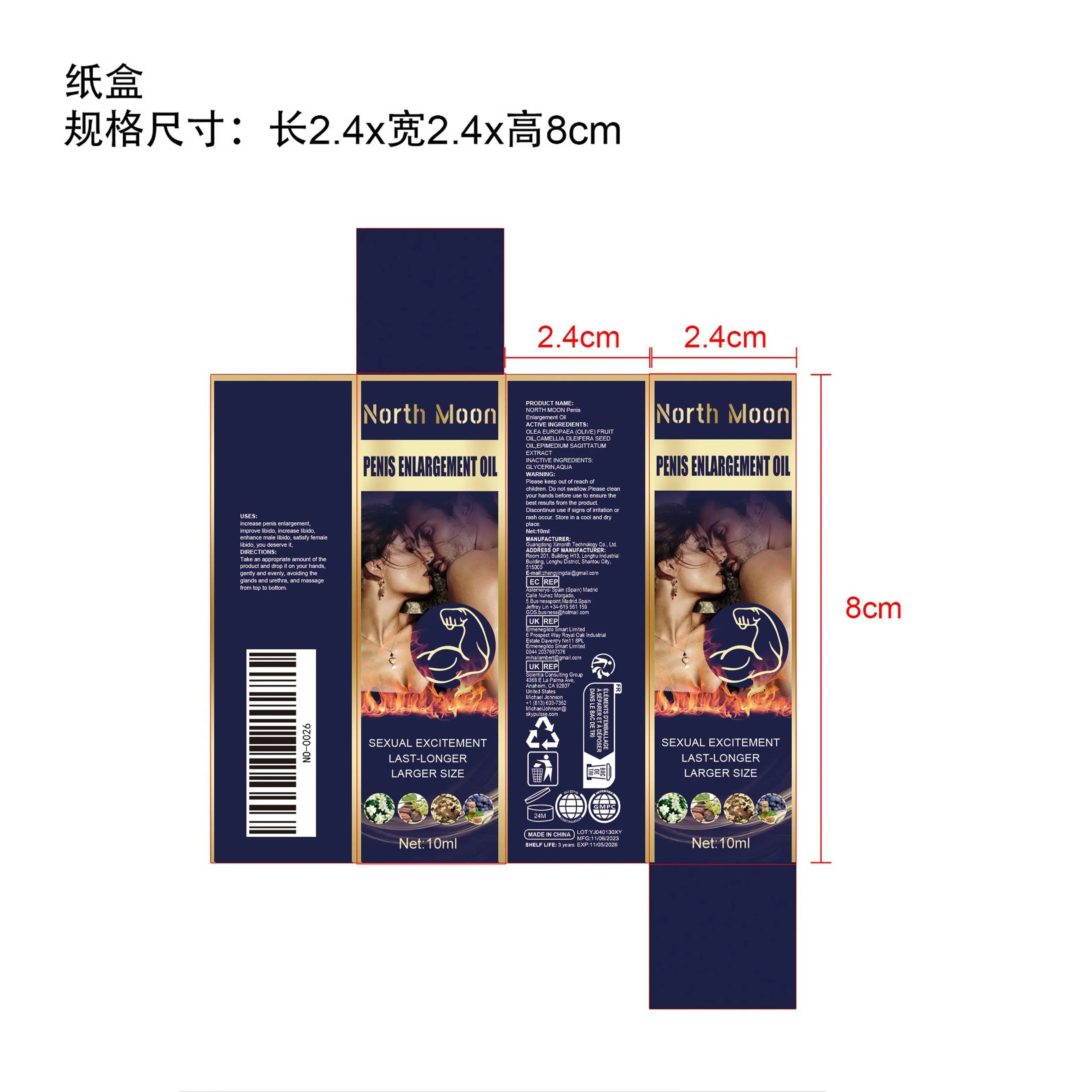 DRUG LABEL: NORTH MOON Penis Enlargement Oil
NDC: 84660-059 | Form: OIL
Manufacturer: Guangdong Ximonth Technology Co., Ltd.
Category: otc | Type: HUMAN OTC DRUG LABEL
Date: 20241102

ACTIVE INGREDIENTS: OLEA EUROPAEA (OLIVE) FRUIT OIL 3 mg/10 mg; EPIMEDIUM SAGITTATUM TOP 1.5 mg/10 mg; CAMELLIA OLEIFERA SEED OIL 1 mg/10 mg
INACTIVE INGREDIENTS: AQUA 3 mg/10 mg; GLYCERIN 1.5 mg/10 mg

ACTIVE INGREDIENTS

OLEA EUROPAEA (OLIVE) FRUIT OIL,CAMELLIA OLEIFERA SEED OIL,EPIMEDIUM SAGITTATUM TOP

PURPOSE

Increase penis enlargement, improve libido,increase libido, enhance male libido,satisfy female libido, you deserve it.

USES

Take an appropriate amount of the product and drop it on your hands, gently and evenly, avoiding the glands and urethra, and massage from top to bottom.

WARNING

Please keep out of reach of children. Do not swallow.Please clean your hands before use to ensure the best results from the product. Discontinue use if signs of irritation or rash occur. Store in a cool and dry place.

STOP USE

Discontinue use if signs of irritation or rash occur.

DO NOT USE

Discontinue use if signs of irritation or rash occur.

KEEP OUT OF REACH OF CHILDREN

Please keep out of reach of children.Do not swallow.

STORAGE AND HANDLING

Store in a cool and dry place

INACTIVE INGREDIENT

GLYCERIN,AQUA